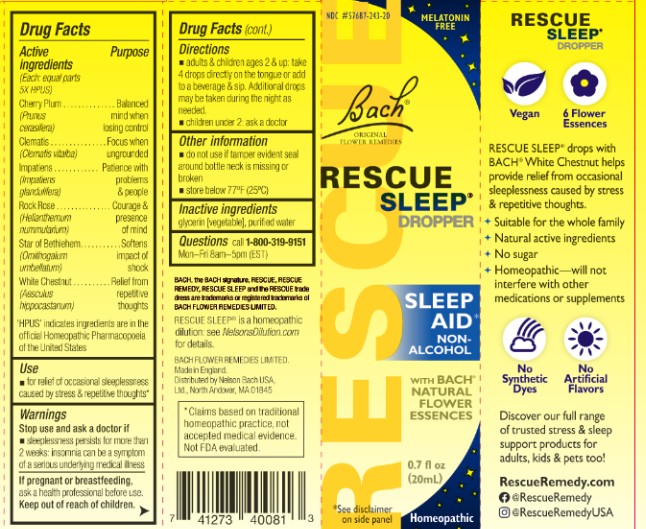 DRUG LABEL: Rescue Sleep
NDC: 57687-243 | Form: SOLUTION
Manufacturer: Nelson Bach USA Limited
Category: homeopathic | Type: HUMAN OTC DRUG LABEL
Date: 20251124

ACTIVE INGREDIENTS: HELIANTHEMUM NUMMULARIUM FLOWER 5 [hp_X]/0.095 mL; CLEMATIS VITALBA FLOWER 5 [hp_X]/0.095 mL; IMPATIENS GLANDULIFERA FLOWER 5 [hp_X]/0.095 mL; PRUNUS CERASIFERA FLOWER 5 [hp_X]/0.095 mL; ORNITHOGALUM UMBELLATUM WHOLE 5 [hp_X]/0.095 mL; AESCULUS HIPPOCASTANUM FLOWER 5 [hp_X]/0.095 mL
INACTIVE INGREDIENTS: GLYCERIN; WATER

Rescue Sleep®
Dropper

ACTIVE INGREDIENT

Active ingredients Each 5× (HPUS) | Purpose
White Chestnut (Aesculus hippocastanum) | Relief from repetitive thoughts
Rock Rose (Helianthemum nummularium) | Courage and presence of mind
Clematis (Clematis vitalba) | Focus when ungrounded
Impatiens (Impatiens glandulifera) | Patience with problems and people
Cherry Plum (Prunus cerasifera) | Balanced mind when losing control
Star of Bethlehem (Ornithogalum umbellatum) | Softens impact of shock

Use

- for relief of occasional sleeplessness caused by stress and repetitive thoughts

Warnings

Stop use and ask a doctor if sleeplessness persists for more than two weeks: insomnia can be a symptom of serious underlying medical illness

PREGNANCY OR BREAST FEEDING

If pregnant or breast-feeding, ask a health professional before use.

Keep out of reach of children.

Directions

- adults and children age 2 and up: take 4 drops directly on the tongue or 4 drops in water and sip at intervals. Additional drops may be taken during the night as needed.
- children under 2: ask a doctor

Other information

- store below 77°F (25°C)
- do not use if tamper evident seal is broken
- active ingredients made according to the Homeopathic Pharmacopoeia of the United States (HPUS)

INACTIVE INGREDIENT

glycerin [vegetable], purified water

QUESTIONS

Call 1-800-319-9151

Mon-Fri 8am-5pm (EST)

PACKAGE LABEL

Rescue Sleep Dropper